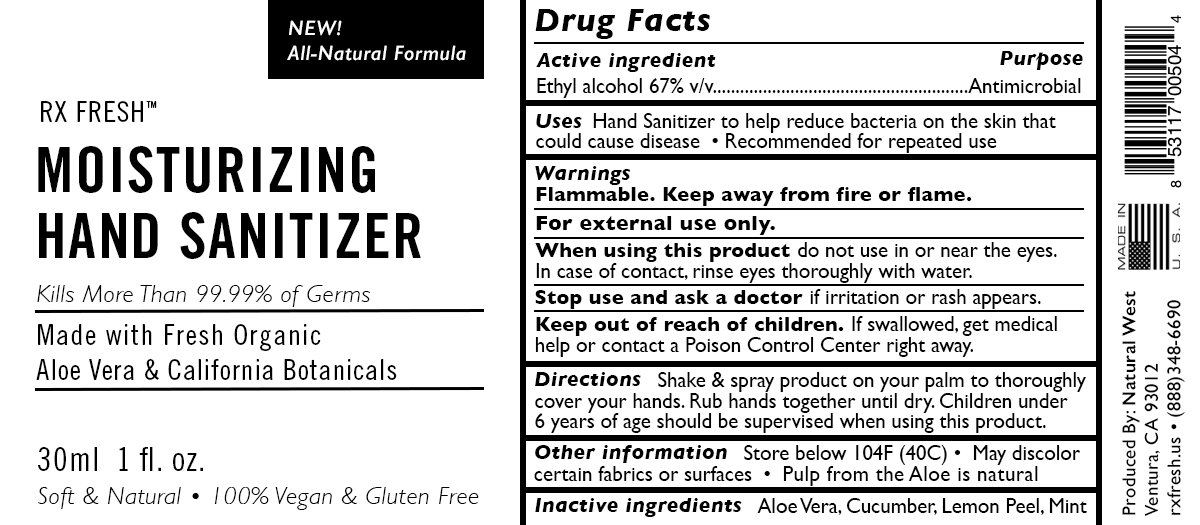 DRUG LABEL: RX FRESH Moisturizing Hand Sanitizer
NDC: 73748-001 | Form: SPRAY
Manufacturer: Natural West
Category: otc | Type: HUMAN OTC DRUG LABEL
Date: 20200318

ACTIVE INGREDIENTS: ALCOHOL 0.67 mL/1 mL
INACTIVE INGREDIENTS: CUCUMBER; ALOE VERA LEAF; MINT; LEMON PEEL

RX FRESH Moisturizing Hand Sanitizer

Active Ingredient

Ethyl Alcohol 67% v/v

Purpose

Antimicrobial

Uses

Hand Sanitizer to help reduce bacteria on the skin that could cause disease. Recommended for repeated use.

Warnings

- Flammable
- Keep away from fire or flame
- For external use only
- When using this product do not use in or near the eyes. In case of contact, rinse eyes thoroughly with water
- Stop use and ask a doctor if irritation or rash appears
- Keep out of reach of children. If swallowed, get medical help or contact a Poison Contol Center right away.

Keep Out of Reach of Children

If swallowed, get medical help or contact a Poison Control Center right away.

Inactive Ingredients

Aloe Vera, Cucumber, Lemon Peel, Mint

Directions

- Shake and spray product on your palm to thoroughly cover your hands.
- Rub hands together until dry.
- Children under 6 years of age should be supervised when using this product.

Other Information

- Store below 104F (40C)
- May discolor certain fabrics or surfaces
- Pulp from aloe is natural